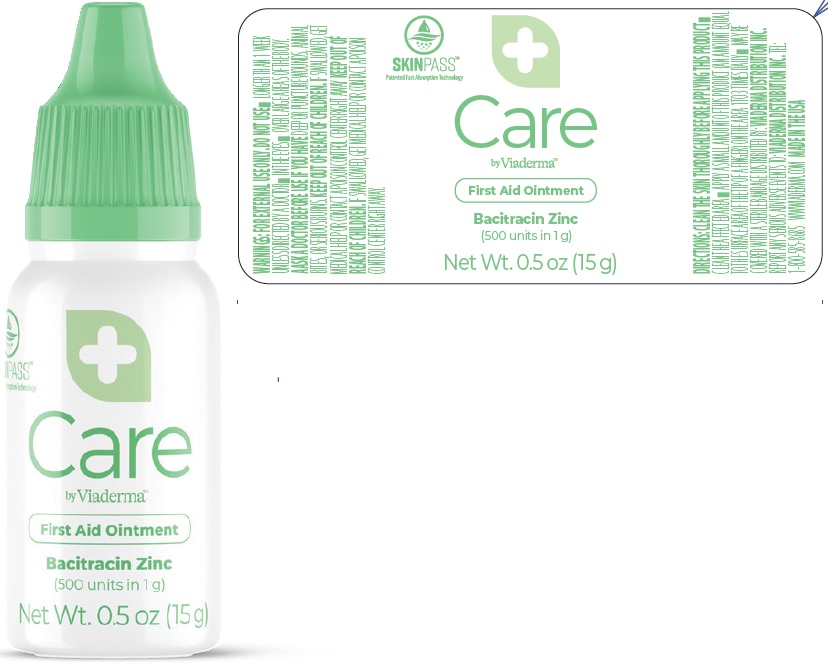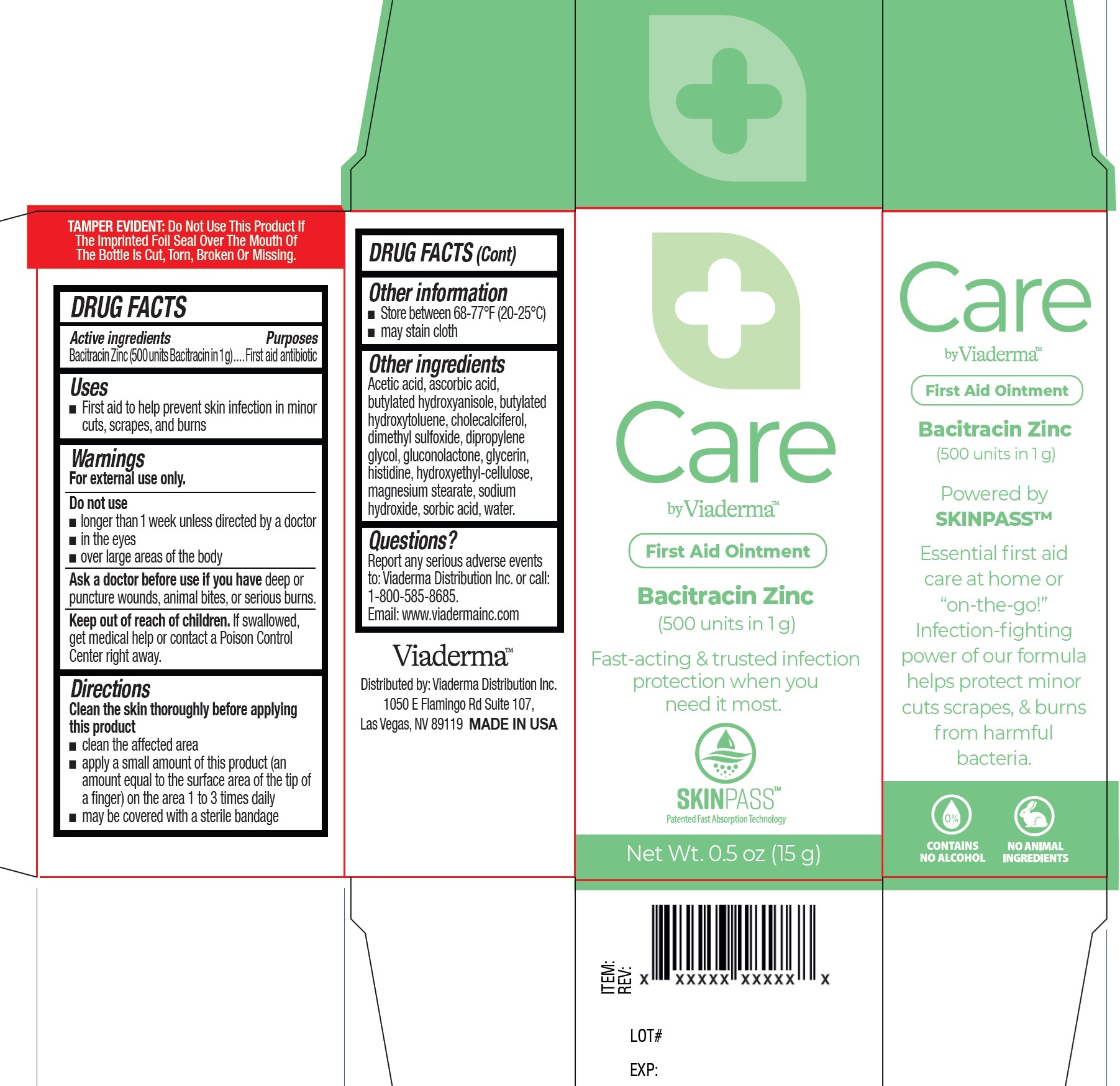 DRUG LABEL: Viaderma Care First Aid
NDC: 71262-015 | Form: OINTMENT
Manufacturer: ViaDerma Distribution, Inc.
Category: otc | Type: HUMAN OTC DRUG LABEL
Date: 20251002

ACTIVE INGREDIENTS: BACITRACIN ZINC 500 U/1 g
INACTIVE INGREDIENTS: ACETIC ACID; ASCORBIC ACID; BUTYLATED HYDROXYANISOLE; BUTYLATED HYDROXYTOLUENE; CHOLECALCIFEROL; DIMETHYL SULFOXIDE; DIPROPYLENE GLYCOL; GLUCONOLACTONE; GLYCERIN; HISTIDINE; HYDROXYETHYL CELLULOSE, UNSPECIFIED; MAGNESIUM STEARATE; SODIUM HYDROXIDE; SORBIC ACID; WATER

Viaderma Care First Aid Ointment

Active ingredients

Bacitracin Zinc (500 units Bacitracin in 1 g)

Purposes

First aid antibiotic

Uses

- First aid to help prevent skin infection in minor cuts, scrapes, and burns

Warnings

For external use only.

Do not use

- longer than 1 week unless directed by a doctor
- in the eyes
- over large areas of the body

Ask a doctor before use if you have

deep or puncture wounds, animal bites, or serious burns.

Keep out of reach of children.

If swallowed, get medical help or contact a Poison Control Center right away

Directions

Clean the skin thoroughly before applying this product

- clean the affected area
- apply a small amount of this product (an amount equal to the surface area of the tip of a finger) on the area 1 to 3 times daily
- may be covered with a sterile bandage

Other information

- Store between 68-77°F (20-25°C)
- may stain cloth

Other ingredients

Acetic acid, ascorbic acid, butylated hydroxyanisole, butylated hydroxytoluene, cholecalciferol, dimethyl sulfoxide, dipropylene glycol, gluconolactone, glycerin, histidine, hydroxyethyl-cellulose, magnesium stearate, sodium hydroxide, sorbic acid, water.

Questions?

Report any serious adverse events
to: Viaderma Distribution Inc. or call:
1-800-585-8685.
Email: www.viadermainc.com